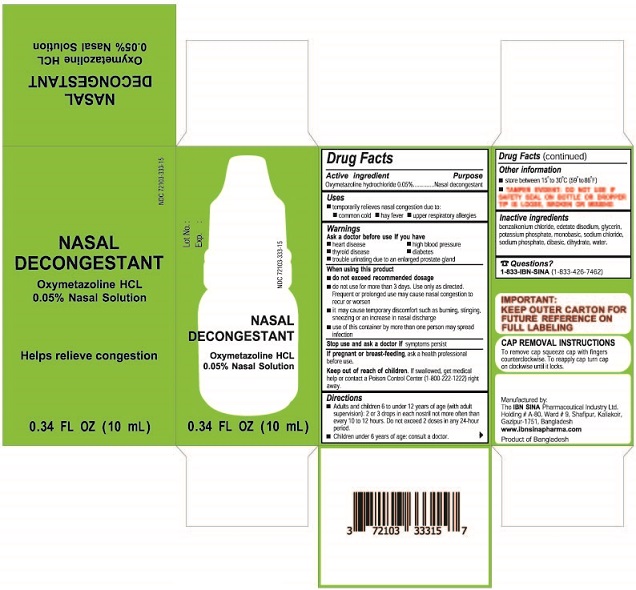 DRUG LABEL: Nasal Decongestant
NDC: 72103-333 | Form: SOLUTION/ DROPS
Manufacturer: THE IBN SINA PHARMACEUTICAL INDUSTRY LTD.
Category: otc | Type: HUMAN OTC DRUG LABEL
Date: 20190312

ACTIVE INGREDIENTS: OXYMETAZOLINE HYDROCHLORIDE 0.05 g/100 mL
INACTIVE INGREDIENTS: BENZALKONIUM CHLORIDE; EDETATE DISODIUM; SODIUM CHLORIDE; SODIUM PHOSPHATE, DIBASIC, DIHYDRATE; POTASSIUM PHOSPHATE, MONOBASIC; GLYCERIN; WATER

IBN OXYMETAZOLINE NASAL SOLUTION

Drug Facts

Active ingredient

Oxymetazoline hydrochloride 0.05%

Purpose

Nasal decongestant

Uses

- temporarily relieves nasal congestion due to:
- common cold
- hay fever
- upper respiratory allergies

Warnings

Ask a doctor before use if you have

- heart disease
- high blood pressure
- thyroid disease
- diabetes
- trouble urinating due to an enlarged prostate gland

When using this product

- do not exceed recommended dosage
- do not use for more than 3 days. Use only as directed. Frequent or prolonged use may cause nasal congestion to recur or worsen
- it may cause temporary discomfort such as burning, stinging, sneezing or an increase in nasal discharge
- use of this container by more than one person may spread infection

Stop use and ask a doctor if symptoms persist

PREGNANCY OR BREAST FEEDING

If pregnant or breast-feeding, ask a health professional before use.

Keep out of reach of children. If swallowed, get medical help or contact a Poison Control Center (1-800-222-1222) right away.

Directions

- Adults and children 6 to under 12 years of age (with adult supervision): 2 or 3 drops in each nostril not more often than every 10-12 hours. Do not exceed 2 doses in any 24-hour period.
- Children under 6 years of age: consult a doctor.

Other information

- store between 15° to 30°C (59° to 86°F)
- TAMPER EVIDENT: DO NOT USE IF SAFETY SEAL ON BOTTLE OR DROPPER TIP IS LOOSE, BROKEN OR MISSING

Inactive ingredients

benzalkonium chloride, edetate disodium, glycerin, potassium phosphate monobasic, sodium chloride, sodium phosphate dibasic dihydrate, water.

Questions?

1-833-IBN-SINA (1-833-426-7462)

Manufactured by:

The IBN SINA Pharmaceutical Industry Ltd.

Holding # A-80, Ward # 9, Shafipur, Kaliakoir,

Gazipur-1751, Bangladesh

www.ibnsinapharma.com

Product of Bangladesh

PACKAGE LABEL

NDC 72103-333-15

NASAL DECONGESTANT

Oxymetazoline HCL 0.05% Nasal Solution

Helps relieve congestion

0.34 FL OZ (10 mL)